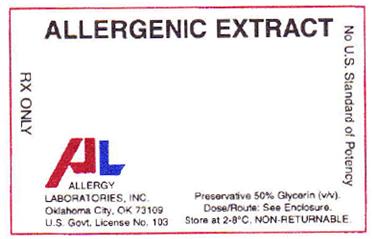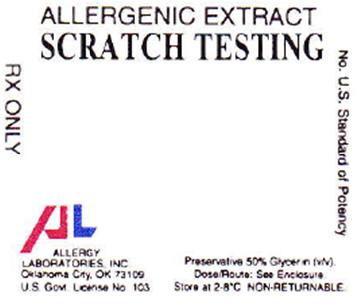 DRUG LABEL: APPLE
NDC: 54575-335 | Form: INJECTION, SOLUTION
Manufacturer: Allergy Laboratories, Inc.
Category: prescription | Type: HUMAN PRESCRIPTION DRUG LABEL
Date: 20110311

ACTIVE INGREDIENTS: APPLE 1 g/20 mL
INACTIVE INGREDIENTS: SODIUM CHLORIDE 0.166 g/100 mL; SODIUM BICARBONATE 0.091 g/100 mL; WATER; GLYCERIN 50 mL/100 mL

Allergenic Extracts

Allergenic Extracts

Directions for Use

WARNINGS

This product is intended for use by physicians who are experienced in the administration of allergenic extracts and the emergency care of anaphylaxis, or for use under the guidance of an allergy specialist.

Patients should be instructed to recognize adverse reaction symptoms and cautioned to contact physicians’ office if reaction symptoms occur. As with all allergenic extracts, severe systemic reactions may occur. In certain individuals these life threatening reactions may be fatal. Patients should be observed for at least 20 to 30 minutes following treatment and emergency measures as well as personnel trained in their use should be immediately available in the event of a life threatening reaction. Serious adverse reactions can be reported to the US Food and Drug Administration MedWatch, 5600 Fishers Lane, Rockville, Maryland 20852-9787, (800) FDA-1088, or www.fda/gov/medwatch.

This product should not be injected intravenously. Patients who are taking non-selective beta blockers may be more reactive to allergens given for testing and may be unresponsive to the usual doses of epinephrine used to treat allergic reactions. Refer to the Warnings, Precautions, Adverse Reactions and Dosage sections below.

DESCRIPTION

Therapeutic extracts (concentrates) are designed primarily for the physician equipped to prepare dilutions and mixtures as necessary. Allergenic Extracts are manufactured from various biological allergenic source materials including pollens, molds, epidermals, insects, food and environmental inhalants. The extraction is performed in a glycerin solution and the resulting concentration is expressed as weight to volume (w/v) ratio. This is the weight of dry pollen in grams to volume of glycerin extracting solution in milliliters. Extracts are filtered and sterile filled. Tests include those for safety and sterility. The route of administration is subcutaneous. Scratch diagnostic extracts are of the same therapeutic extract formulation and their route of administration is percutaneous. Intradermal diagnostic extracts are dilutions of the therapeutic extracts using Sterile Diluent for Allergenic Extract.

Inactive ingredients:
Therapeutic and Scratch extracts: | Intradermal 1:500 v/v (foods) | Intradermal 1:1,000 v/v (pollens, molds, epidermals, inhalants)
Glycerin, USP, 50% v/v | Glycerin, USP, 0.1% v/v | Glycerin, USP, 0.05% v/v
Sodium chloride, USP, 0.166% w/v | Sodium chloride, USP, 0.9% w/v | Sodium chloride, USP, 0.9% w/v
Sodium bicarbonate, USP, 0.091% w/v | Sodium bicarbonate, USP, 0.000182% w/v | Sodium bicarbonate, USP, 0.000091% w/v
 | Phenol, USP, 0.4% w/v | Phenol, USP, 0.4% w/v
Sterile Diluent for Allergenic Extract:
Normal Saline with Phenol: | Human Serum Albumin: | Glycerin, USP, 50% w/v
Sodium chloride, USP 0.9% w/v | Sodium chloride, USP 0.9% w/v | Sodium bicarbonate, USP 0.091% w/v
Phenol, USP 0.4% w/v | Phenol, USP 0.4% w/v | Sodium chloride, USP 0.166% w/v
Water for Injection, USP q.s. | Normal Serum Albumin (Human), 0.03% w/v | Water for Injection, USP, q.s.
Air replaced with Nitrogen, NF | Water for Injection, USP q.s.
 | Air replaced with Nitrogen, NF

The following allergenic extracts are designated and labeled “FOR DIAGNOSTIC USE ONLY”. Data to support the therapeutic use of these extracts has not been established: Coffee Cottonseed Flaxseed Housefly Mosquito

The strength of Standardized Short Ragweed and Ragweed Mix, Giant and Short extracts is described (in addition to w/v) as antigen E content. The concentration of antigen E per milliliter of the final preparation as determined by radial immunodiffusion (RID). The antigen E content of an extract is influenced by several variables. These include antigen E content of the pollen, nature of extracting solutions, ratio of pollen weight to volume of extracting solution and storage conditions. Variables which influence antigen E stability during storage conditions include nature of the solvent, antigen E concentration and storage temperature. Glycerin is a stabilizer of antigen E and other allergens.

CLINICAL PHARMACOLOGY

Allergenic extracts for diagnostic testing produce erythema or erythema and wheal reactions in patients with significant IgE-mediated sensitivity to the relevant allergen. This allergic inflammatory response, although not completely understood, is thought to begin with the reaction of antigen with IgE on the surface of basofils, or mast cells, which initiates a series of biochemical events resulting in the production of histamine and other mediators. These, in turn, produce the immediate-type “wheal and flare” skin reaction. The more mediator released, the larger the reaction. Because of a variety of factors, including the types of allergen extracts, delayed skin reactions can occur and usually disappear within a couple of days. The type of extract, size of the reaction and timing of the reaction are all factors used in determining a patient’s sensitivity to an allergen.

Allergen immunotherapy (also known as desensitization, hyposensitization, allergy vaccination, or allergy shots) involves treating a patient with increasing dosage of the allergens to which he is allergic, eventually reaching a dose plateau whereas the patient experiences an increased tolerance upon re-exposure to the allergens. The patient may or may not need to receive continued treatment to demonstrate the desensitization. The exact mechanisms of reaction of desensitization with allergens, which involve the allergen, IgE and IgG antibodies, mast cells and basophils and possibly other mediators, are not completely understood. However, efficacy has been shown in numerous well-controlled studies using specific common allergens.

The goals of allergen immunotherapy are to decrease the production of IgE antibodies, initiate the production of IgG antibodies and stabilize mast cells and basophils. Overproduction of IgE in response to an allergen can induce other cells, particularly mast cells and basophils, to initiate a complex chain reaction that results in allergy symptoms. Numerous IgE receptor sites are located on mast cells as well as basophil cells. These cells are among the first cells to be encountered by the antigen. They contain potent chemical mediators (histamine and leukotriene, for example) of inflammation that are released when IgE and a specific allergen cross-link on the cell surface. The release of the chemical mediators results in inflammation and allergy symptoms. As a response to immunotherapy, the production of IgG is believed to work by blocking IgE from binding to mast cells and basophils. Thus IgG, the blocking antibody, may prevent the release of chemical mediators that produce allergy symptoms.

INDICATIONS AND USAGE

Immunotherapy using allergenic extracts is indicated for use in patients with severe allergy symptoms (hay fever, rhinitis, etc.) to pollens, molds, insects, animal danders and various other allergens. Immunotherapy is intended for patients whose symptoms are not satisfactorily controlled by avoidance of the offending allergen or by the use of symptomatic medications. Treatment uses only those specific allergens that the patient is sensitive to based on diagnostic tests and medical history. It is not intended for treatment of patients who do not manifest immediate hypersensitivity reactions to the allergenic extract following skin testing.

CONTRAINDICATIONS

There are no known absolute contraindications to diagnostic testing or hyposensitization with allergen immunotherapy.

Patients with cardiovascular disease or pulmonary disease such as symptomatic asthma, and/or who are receiving cardiovascular drugs such as beta blockers, may be at higher risk for severe adverse reactions. These patients may also be more refractory to the normal anaphylaxis treatment regimen.

Immunotherapy is not generally indicated when the offending allergen(s) can be effectively eliminated or minimized by environmental control. There are differences of opinion on the possibility of routine immunizations exacerbating autoimmune diseases. The evidence has been inconclusive. Therefore, caution should be exercised in administering immunotherapy to patients with other immunologic diseases and only administered if the risk from exposure to the allergen is greater than the risk of exacerbating the underlying disorder. Injections should be avoided in patients with a bleeding tendency.

WARNINGS

See boxed WARNINGS at the beginning of this information sheet.

Do not administer allergenic extract injections intravenously. Patients should always be observed for at least 20 to 30 minutes after any skin test or injection. Concentrated allergenic extracts should be diluted with Sterile Diluent for Allergenic Extract prior to use for intradermal testing and for immunotherapy preparation. Systemic reactions may occur infrequently and may range from mild exaggeration of the patient’s allergic symptoms to urticaria, rhinitis, conjunctivitis, angioedema, cough, wheezing, fainting, pallor, bradycardia, hypotension, or even, in extremely sensitive individuals, to anaphylactic shock and death. Have epinephrine 1:1,000 readily available in case of a reaction. Emergency measures and personnel trained for medical emergencies should be immediately available in the event of a life-threatening reaction. Patients with unstable asthma or steroid dependent asthmatics and patients with underlying cardiovascular disease are at greater risk. Patients taking beta-blocker medication may not respond to the usual dose of epinephrine.

Diagnostic testing as well as immunotherapy should be temporarily withheld from patients or the dose reduced until cause of reaction is evaluated by prescribing physician if any of the following conditions exist: (1) severe symptoms of rhinitis and/or asthma, (2) infection or flu accompanied by fever, (3) exposure to excessive amounts of clinically relevant allergen prior to a scheduled injection, and (4) systemic reaction to previous injection.

PRECAUTIONS

(1) GENERAL

The presence of asthmatic signs and symptoms may be an indicator of severe reaction following allergen injections. Any evidence of a local or generalized reaction requires a dose reduction during the initial stages of immunotherapy, as well as during maintenance therapy. Patient reactions to previous injections should be reviewed before each new injection and a conservative dosage schedule should be followed until a pattern of local responses is established which can be used to monitor increases in dosage. Patients should be observed in the office for at least 20 to 30 minutes after each treatment injection and instructed to seek medical attention if symptoms of a systemic reaction occur. Most severe reactions will occur within this time period, and rapid treatment measures should be initiated (see ADVERSE REACTIONS). In rare circumstances, a patient may have systemic reactions to minute doses of antigen and does not demonstrate increasing tolerance to injections after several months of treatment. If systemic reactions or excessive local responses occur persistently at very small doses, efforts at immunotherapy should be stopped.

When changing lots of extracts, even though the formulation may be the same, the first dose should not exceed 50% of the previous dose as the extract may have lost potency over time and a fresh extract could have an effective potency that is substantially greater than that of the old extract. Aseptic technique should always be used when injections of allergenic extracts are administered.

(2) INFORMATION FOR PATIENTS

Patients should be instructed to remain in the office for 20 to 30 minutes after each injection to monitor for adverse reactions. Patients should be instructed to describe any active allergic symptoms such as rhinitis, wheezing, dyspnea, etc. prior to injection including any late reactions from previous administration.

(3) DRUG INTERACTIONS

Beta-Blockers: Patients who are taking non-selective beta blockers may be more reactive to allergens given for testing and may be unresponsive to the usual doses of epinephrine used to treat allergic reactions. Patients with cardiovascular diseases and/or pulmonary diseases such as symptomatic unstable, steroid-dependent asthma, and/or those who are receiving cardiovascular drugs such as beta-blockers, may be at higher risk for severe adverse reactions.

Antihistamines can significantly inhibit the immediate skin test reactions. If long acting antihistamines have been taken recently, it is recommended that they should be stopped for the following minimum intervals before skin testing is performed: 1 week for hydroxyzine or cetirizine; 4 to 7 days for loratadine; 3 to 4 days for fexofenadine; and 24 to 48 hours for other sustained release antihistamines.

(4) CARCINOGENISIS, MUTAGENESIS, IMPAIRMENT OF FERTILITY

Long term studies with allergenic extracts have not been conducted in animals to determine their potential for carcinogenesis, mutagenesis, or impairment of fertility.

(5) PREGNANCY – CATEGORY C

Animal reproduction studies have not been conducted with allergenic extracts. It is also not known whether allergenic extracts can cause fetal harm when administered to a pregnant woman or if they can affect reproduction capacity. The physician must weigh the benefits of immunotherapy against the risk of anaphylactic reactions that could result in harm to the mother and/or fetus. Hyposensitization should be used during pregnancy only if clearly necessary and administered cautiously.

(6) NURSING MOTHERS

It is not known if allergenic extracts appear in human milk. Because many drugs are excreted in human milk, caution should be exercised when allergenic extracts are administered to a nursing woman.

(7) PEDIATRIC USE

Extracts have not been studied in children, so the safety in children has not been established. Doses of allergenic extracts for children are generally the same as those for adults. In the case of large doses, the amount of extract given to a child may be modified so that the discomfort of the injection is minimized.

ADVERSE REACTIONS

(1) Local Reactions - A mild burning immediately after the injection is to be expected; this usually subsides in 10 to 20 seconds. Reactions at the site of injection (erythema, swelling, pruritus) may be immediate or delayed. Immediate wheal and erythema reactions are ordinarily of little consequence; but if very large, may be the first manifestation of a systemic reaction. Delayed reactions start several hours after injection with local edema, erythema, itching or pain. The reactions are most apparent 24 hours after injection and usually require no treatment. Antihistamines may be administered orally if necessary. Large local reactions may be treated by local applications of cold, wet dressings and/or the use of oral antihistamines. These reactions should be considered a warning of possible severe systemic reaction and need for temporarily reduced dosage. In such cases the next therapeutic dose should be reduced to the last dose which did not elicit a reaction and subsequent doses increased more slowly.

(2) Systemic Reactions - Most severe systemic reactions occur within 30 minutes of injection but may occur at anytime subsequent to treatment. Symptoms may range from mild to life-threatening (due to anaphylaxis). Systemic reactions are characterized by one or more of the following symptoms: sneezing, mild to severe generalized urticaria, itching other than at the injection site, extensive or generalized edema, wheezing, asthma, dyspnea, cyanosis, tachycardia, lacrimation, marked perspiration, cough, hypotension, syncope and upper airway obstruction. Symptoms may progress to anaphylactic shock and death.

If a systemic or anaphylactic reaction does occur, apply a tourniquet above the site of injection and inject 1:1,000 epinephrine-hydrochloride intramuscularly into the opposite arm or gluteal area. Loosen the tourniquet at least every 10 minutes. Do not obstruct arterial blood flow with the tourniquet.

1:1,000 EPHEDRINE DOSAGE:

ADULT: 0.3 mL to 0.5 mL should be injected intramuscularly or subcutaneously. Repeat in 5 to 10 minutes if necessary.

PEDIATRIC: Suggested dosage for infants to 2 years of age is 0.05 mL to 0.1 mL; for children 2 to 6 years, 0.15 mL; and children 6 to 12 years, 0.2 mL.

Doses may be repeated every 20 minutes, depending on the severity of the condition and the response of the patient. After administration of epinephrine, profound shock or vasomotor collapse should be treated with intravenous fluids, and vasoactive drugs if necessary. An open airway should be insured. Give oxygen by mask. Intravenous antihistamine, inhaled bronchodilators, theophyllin and/or adrenal corticosteroids may be used if necessary after adequate epinephrine and circulatory support has been given. Emergency resuscitation measures and personnel trained in their use must be available immediately in the event of a serious systemic or anaphylactic reaction not responsive to the above measures.

If the patient is continued on immunotherapy, a decrease of at least 50% in the next dose should follow serious systemic reactions. Increases in dose should be made cautiously. Repeated systemic reactions are sufficient reason for discontinuation of increased dosages.

(3) To report suspected ADVERSE REACTIONS, contact Allergy Laboratories, Inc. 800-654-3971 or FDA 800-FDA-1088 or www.fda/gov/medwatch.

OVERDOSAGE

Signs and symptoms of overdose are typically local and systemic reactions. For a description and management of overdose reactions, see ADVERSE REACTIONS.

DOSAGE AND ADMINISTRATION

Parenteral drug products should be inspected visually for particulate matter and discoloration prior to administration, whenever solution and container permit.

Allergenic extracts may be administered for diagnostic testing or therapeutic purposes. The dosage will depend on the particular use of the extract.

General: When used for diagnostic testing to determine a patient’s sensitivity to specific antigens and aid in the diagnosis and treatment of atopic disease, the recommended procedure is to initially perform puncture tests, then follow with intradermal tests. The number of skin tests applied at one time will depend on the particular patient and their allergic history. These tests should be performed and observed in 15 to 20 minutes. Additional tests may be applied in sequence. Perform tests on the anterolateral aspect of the upper arm on an area that permits the effective application of a tourniquet proximal to the site of the test. The skin at the site of injection should be disinfected with rubbing alcohol before testing. A positive reaction usually develops in 15 to 20 minutes. The positive response is a wheal and flare reaction that is larger than the negative control and evaluated based on the size of the reaction.

Controls: A negative control containing the same solution that the extract was prepared in should be applied to a test site in the same manner as the tests being performed. Histamine phosphate should be used as a positive control for evaluation of skin testing. Refer to manufacturers directions provided with Histamine phosphate for recommended dosage and administration.

Percutaneous testing: In general, skin is scratched, punctured or pricked just before the allergen is applied or through a drop of test allergen which is placed on the skin. There are several devices available for this technique. Refer to the device manufacturers instructions for proper use. Test areas should be no closer than 4-5 cm apart to avoid the interference of multiple reactions. Clean test areas with alcohol and air dry. Place the allergen on the volar surface of the patient’s forearm, upper arm, or back.

1. For puncture tests, apply one drop of extract to the skin. Pierce the drop of extract and skin using a sterile hypodermic needle or vaccinating needle. Maintain the needle perpendicular to the skin surface and rock the needle back and forth to produce a small hole without bleeding. Do not rotate or gouge the needle. Remove needle from skin and wipe excess extract from skin surface.

2. For scratch tests using a scarifier or needle: make a scratch 1/16 inch long on the epidermis penetrating the outer cornified area but being careful not to draw blood. Apply one drop of allergen to the scratch or puncture.

Intracutaneous (Intradermal) testing: If puncture test is negative, proceed with intradermal test. Intradermal tests should not be performed if puncture test is positive. Use a separate sterile syringe (tuberculin type equipped with a 27 gauge by 3/8 inch needle with intradermal bevel) for each antigen. To administer the test, inject 0.02 mL of allergen into the epidermis using dilutions of the concentrated extract; a 1:500 v/v dilution for foods and 1:1,000 v/v dilution for other extracts. If the test has been performed properly, the solution should raise a bleb 2 to 3 mm in diameter. If the bleb does not appear, the injection was made too deeply. To prepare intradermal testing strengths using 1:20 w/v bulk concentrates, use the following example: Add 1 mL of 1:20 w/v to 4 mL diluent to make a 1:100 v/v dilution. Add 1 mL of 1:100 v/v to 4 mL diluent to make a 1:500 v/v dilution. Add 0.5 mL of 1:100 v/v dilution to 4.5 mL diluent to make a 1:1,000 v/v dilution.

Interpretation of results:
Percutaneous tests | Intradermal tests ^1
1+ Erythema with 5mm wheal | 0 <5mm Erythema with a <5mm wheal
2+ Erythema with a 5-10mm wheal | +/- 5-10mm Erythema with a 5-10mm wheal
3+ Erythema with a 10-15mm wheal | 1+ 11-20mm Erythema with a 5-10mm wheal
4+ Erythema with a wheal 15mm or larger with pseudopodia | 2+ 21-30mm Erythema with a 5-10mm wheal
 | 3+ 31-40mm Erythema with a 10-15mm wheal or with pseudopodia
 | 4+ >40mm Erythema with >15mm wheal or with pseudopodia

Immunotherapy:

(1) General: Parenteral drug products should be inspected visually for particulate matter and discoloration prior to administration whenever solution and container permit. Injections are given subcutaneously; preferably in the arm. It is advantageous to give injections in alternate arms. Use sterile precautions and a tuberculin syringe when administering each dose. Allergen immunotherapy is typically initiated with a diluted formulation of allergens prescribed by a physician for administration to a patient. Doses are gradually increased over time and ultimately reach a maintenance dose where the patient is maintained for as long as the physician or patient feels is necessary. The formulation and dosage schedule is determined by the physician and is based on diagnostic testing and patient history. Patients with very high sensitivities should be initiated with lower concentrations (higher dilutions) and may need a very relaxed progression to maintenance doses. Pre-seasonal therapy may be initiated three months before seasonal difficulty begins and brought to maintenance dose and discontinued after that season ends. Perennial therapy (recommended) brings the patient up to tolerated maintenance dose where they remain until improvement of allergic symptoms occurs. Injections may be given at intervals of 4 to 7 days with either therapy.

(2) Suggested dilution series: Concentrated Allergenic Extracts must be diluted with Sterile Diluent for Allergenic Extract before using for immunotherapy. A 1:100,000 v/v dilution of concentrate is usually satisfactory to start treatment. To prepare a 10-fold dilution series from concentrated bulk extract, the following is suggested: Add 1 mL of 1:20 w/v extract to 4 mL diluent to make a 1:100 v/v dilution. Add 0.5 mL of the 1:100 dilution to 4.5 mL of diluent to make a 1:1,000 v/v dilution. Add 0.5 mL of the 1:1,1000 dilution to 4.5 mL diluent to make a 1:10,000 v/v dilution. Add 0.5 mL of the 1:10,000 dilution to 4.5 mL of diluent to make a 1:100,000 v/v dilution. The series may be extended to 1:1,000,000 v/v by preparing one more similar dilution as a precaution for sensitive patients.

(3) Maintenance: The maintenance level is the largest dose tolerated by the patient that relieves symptoms without producing undesirable local or general reactions. After immunotherapy has been established, a maintenance dose should be given at weekly intervals. The interval between maintenance doses can be increased gradually from one week to 10 days, to 2 weeks, 3 weeks, or even 4 weeks as allergy symptoms allow. Repeat maintenance doses at a given interval three or four times to check for continued allergy symptom relief before increasing the interval further. If large local (or systemic) reactions occur at one interval, do not increase the interval. Protection is lost rapidly if the interval between doses is more than 4 weeks. It may not be possible for all patients to reach the maximum dose indicated on the suggested dosage schedule.

(4) Suggested dosage schedule: Because the degree of sensitivity varies in many individuals, the dose and interval may need adjustment and should reflect the patient’s tolerance and response. A dose should never be given until all reactions resulting from a previous dose have entirely disappeared. After a period on immunotherapy, better tolerance may permit a longer interval between injections, or a larger maintenance dose, or both.

1:100,000 v/v |  |  | 1:10,000 v/v |  |  | 1:1,000 v/v |  |  | 1:100 v/v
Dose | Vol. (mL) |  | Dose | Vol. (mL) |  | Dose | Vol. (mL) |  | Dose | Vol. (mL) | Maintenance
1 | 0.02 |  | 8 | 0.02 |  | 13 | 0.02 |  | 19 | 0.02
2 | 0.04 |  | 9 | 0.05 |  | 14 | 0.05 |  | 20 | 0.05 | Continue 0.25 mL of 1:100 v/v weekly.
3 | 0.06 |  | 10 | 0.10 |  | 15 | 0.10 |  | 21 | 0.08
4 | 0.10 |  | 11 | 0.15 |  | 16 | 0.15 |  | 22 | 0.10
5 | 0.15 |  | 12 | 0.25 |  | 17 | 0.20 |  | 23 | 0.15
6 | 0.20 |  |  |  |  | 18 | 0.25 |  | 24 | 0.20
7 | 0.25 |  |  |  |  |  |  |  | 25 | 0.25

(5) Dose adjustments: Since the individual components of the extract are those to which the patient is allergic and to which he will be exposed, typical allergic symptoms may follow shortly after the injection, particularly those experienced by the patient during exposure when the antigen from the environment plus the injected antigen exceeds the patient’s tolerance to the antigen. In such cases, decrease the size of the next scheduled dose by at least one-half of the previous dose.

(6) Administration: Use aseptic precautions when diluting and/or preparing an injection. To avoid cross-contamination, do not use the same needle to withdraw materials from multiple vials. Use a sterile tuberculin syringe (26 or 27 gauge) with a needle at least 5/8” long and graduated in 0.01 mL units to measure each dose.

HOW SUPPLIED

Bulk extract (stock concentrate) in 50% v/v glycerin is supplied in 10 mL, 30 mL, and 50 mL multiple dose vials as well as 2 mL scratch (dropper) vials. Intradermal tests are supplied in 5 mL vials at 1:500 v/v for food extracts and at 1:1,000 v/v for other extracts.

STORAGE

To insure the maximum potency of bulk extract and extract dilutions, it is recommended that they be maintained at a temperature of 2 to 8 degrees Celsius. Do not freeze. Do not use after the expiration date shown on the vial label.

REFERENCES

1. Norman, P.S.: In vivo methods of study of allergy: Skin and Mucosal tests, techniques, and interpretation. In Middleton, E. Jr., Reed, C. E. and Ellis, E.F. (ed): Allergy Principles and Practice, (Vol. 1), p. 258. St. Louis, The C.V. Mosby Co. 1978.

ALLERGY LABORATORIES, INC.
U.S. License # 103
Oklahoma City, OK 73109
(800) 654-3971, (405) 235-1451

Rev. 12/2010

PACKAGE LABEL

PRINCIPAL DISPLAY PANEL
ALLERGENIC EXTRACT

RX ONLY

PACKAGE LABEL

PRINCIPAL DISPLAY PANEL

ALLERGENIC EXTRACT

SCRATCH TESTING

RX ONLY